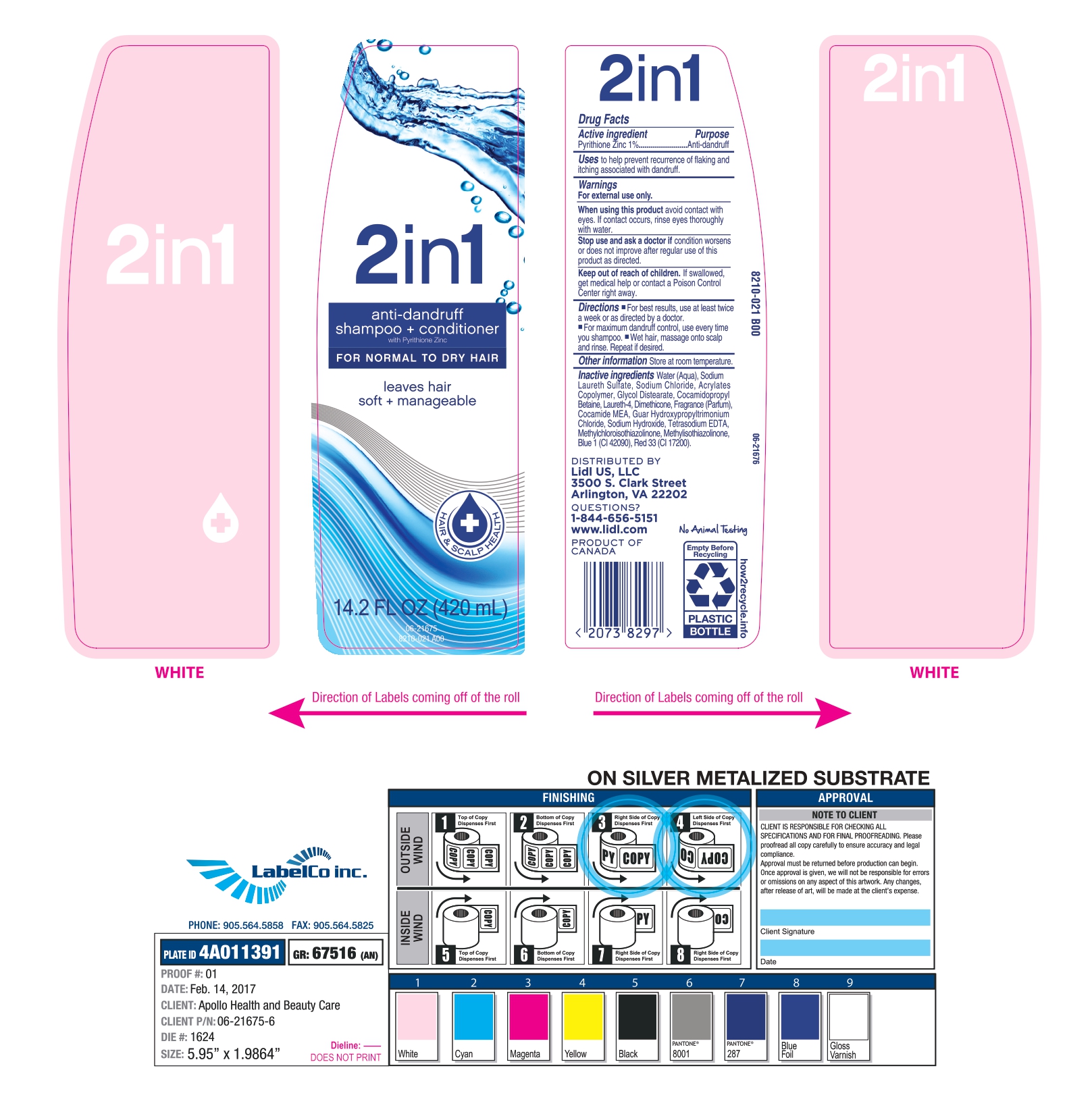 DRUG LABEL: 2 in 1
NDC: 71141-027 | Form: SHAMPOO
Manufacturer: LIDL US LLC
Category: otc | Type: HUMAN OTC DRUG LABEL
Date: 20220912

ACTIVE INGREDIENTS: PYRITHIONE ZINC 10 mg/1 mL
INACTIVE INGREDIENTS: DIMETHICONE; GUAR HYDROXYPROPYLTRIMONIUM CHLORIDE (1.7 SUBSTITUENTS PER SACCHARIDE); METHYLISOTHIAZOLINONE; METHYLCHLOROISOTHIAZOLINONE; FD&C BLUE NO. 1; D&C RED NO. 33; SODIUM LAURETH SULFATE; LAURETH-4; EDETATE SODIUM; COCO MONOETHANOLAMIDE; SODIUM CHLORIDE; METHACRYLIC ACID - ETHYL ACRYLATE COPOLYMER (4500 MPA.S); GLYCOL DISTEARATE; COCAMIDOPROPYL BETAINE; FRAGRANCE CLEAN ORC0600327; SODIUM HYDROXIDE; WATER

71141-027, LIDL US LLC

Active Ingredient.

PYRITHIONE ZINC (1%)

Purpose

Anti dandruff

Uses

To prevent recurrence of flaking and itching associated with dandruff.

Warnings

For external use only

When using this product

Avoid contact with eyes.If contact occurs, rinse eyes thoroughly with water.

Stop use and ask a doctor

if condition worsens or does not improve after regular use of this product as directed.

Keep out of reach of children.

If swallowed, get medical help or contact a Poison Control Center right away.

Directions

- For best resuts, use at least twice a week or as directed by a doctor.
- For maximum dandruff control, use every time you shampoo.
- Wet hair, massage onto scalp and rinse. Repeat if desired.

Other Information

Store at room temperature

Inactive Ingredients

Water (Aqua), Sodium Laureth Sulfate, Sodium Chloride, Acrylates Copolymer, Glycol Distearate, Cocamidopropyl Betaine, Laureth-4, Dimethicone, Fragrance (Parfum), Cocamide MEA, Guar Hydroxypropyltrmonium Chloride, Sodium Hydroxide, Tetrasodium EDTA, Methylchloroisothiazolinone, Methylisothiazolinone, Blue 1 (Cl 42090), Red 33 (Cl 17200).